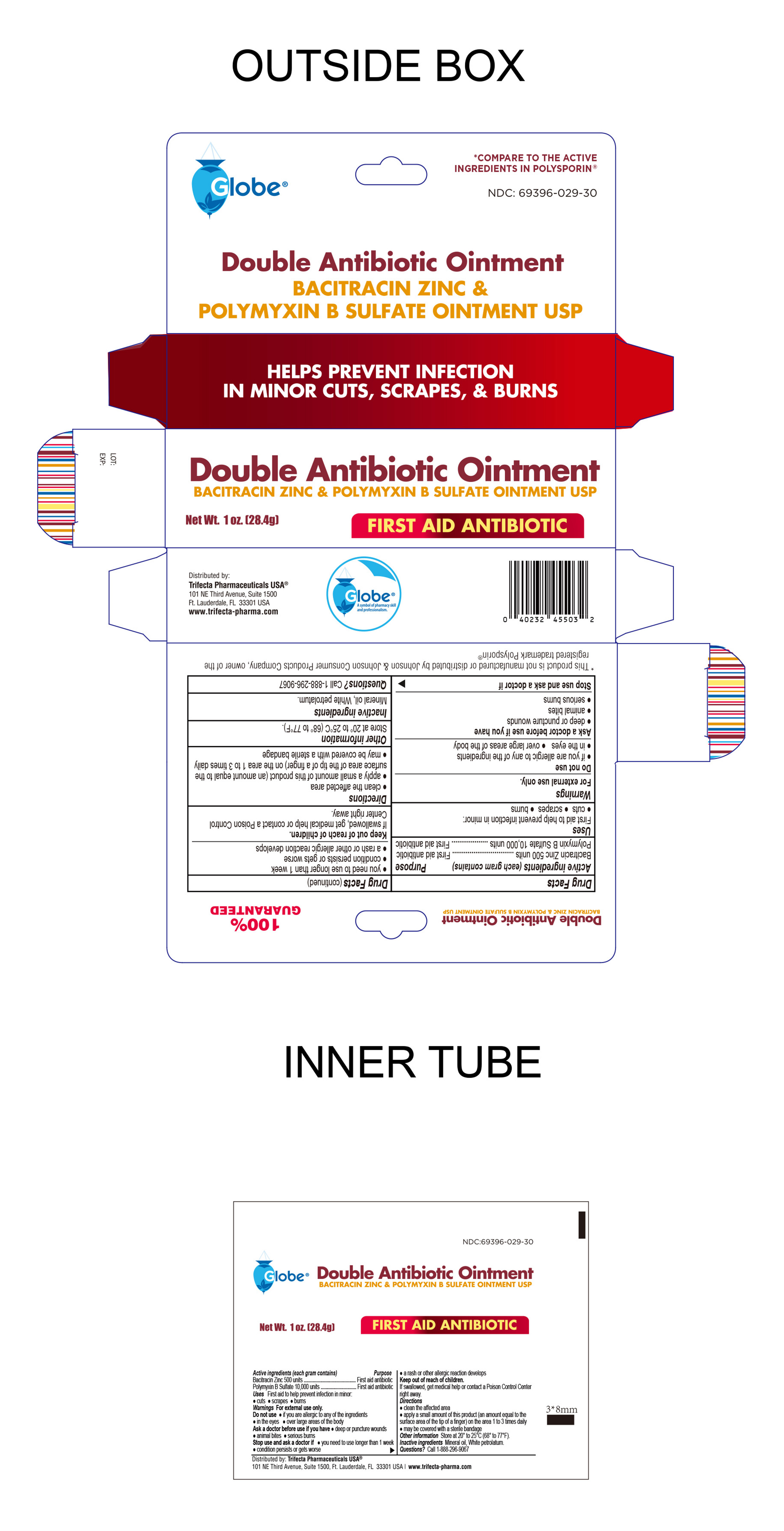 DRUG LABEL: doubleantibioticointment
NDC: 69396-029 | Form: OINTMENT
Manufacturer: Trifecta Pharmaceuticals USA LLC
Category: otc | Type: HUMAN OTC DRUG LABEL
Date: 20251020

ACTIVE INGREDIENTS: POLYMYXIN B SULFATE 10000 [USP'U]/1 g; BACITRACIN ZINC 500 [USP'U]/1 g
INACTIVE INGREDIENTS: MINERAL OIL; WHITE PETROLATUM

Double Antibiotic Ointment

Active Ingredient

Bacitracin Zinc 500 Units

Purpose

First Aid Antibiotic

Active Ingredient

Polymyxin B Sulfate

Purpose

First Aid Antibiotic

Uses

First aid to help prevent infection in minor

- cuts
- scrapes
- burns

Warnings

For External use only.

Do not use

- If you are allergic to any of the ingredients
- in the eyes
- over large areas of the body

Ask a doctor before use if you have:

- deep puncture wounds
- animal bites
- serious burns

Stop use and ask doctor if:

- You need to use longer than 1 week
- Condition persists or gets worse
- rash or other allergic reaction develops

KEEP OUT OF REACH OF CHILDREN

If swallowed, get medical help or contact a Poison Control Center immediately.

Directions:

- Clean the affected area
- Apply a small amount of this product (an amount equal to the surface area of the tip of a finger) on the area 1 to 3 times daily
- May be covered with a sterile bandage

Other Information

Store between 20° to 25°C (68° to 77°F)

Inactive Ingredients

White Petrolatum

Mineral Oil

Questions?

Call 1-888-296-9067

Distributed By:

Trifecta Pharmaceuticals USA™

101 NE Third Avenue, Suite 1500

Ft. Lauderdale, FL, 33301, USA

1-888-296-9067

www.trifecta-pharma.com

*This product is not manufactured or distributed by Johnson & Johnson Consumer Products company, owner of the registered trademark Polysporin®